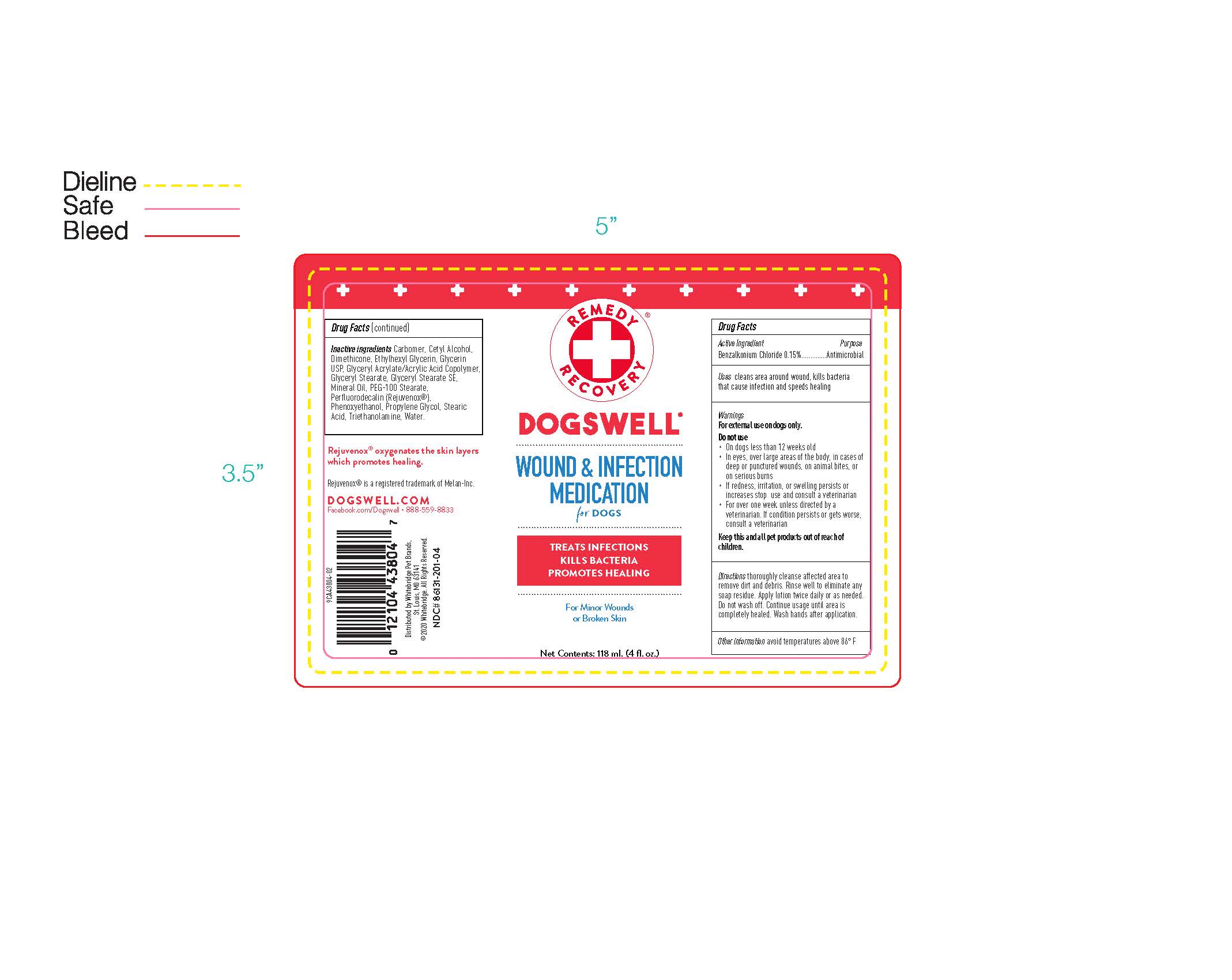 DRUG LABEL: Wound and Infection Medication
NDC: 86131-201 | Form: LOTION
Manufacturer: Whitebridge Pet Brands
Category: animal | Type: OTC ANIMAL DRUG LABEL
Date: 20251223

ACTIVE INGREDIENTS: BENZALKONIUM CHLORIDE 0.15 g/1 g
INACTIVE INGREDIENTS: GLYCERYL MONOSTEARATE; ETHYLHEXYLGLYCERIN; PHENOXYETHANOL; WATER; MINERAL OIL; GLYCERYL STEARATE SE; GLYCERIN; STEARIC ACID; POLYOXYL 100 STEARATE; DIMETHICONE; CETYL ALCOHOL; PERFLUORODIMETHYLCYCLOHEXANE; CARBOMER 940; PROPYLENE GLYCOL; FENOPROP TRIETHANOLAMINE; ACRYLIC ACID

WOUND & INFECTION MEDICATION

DRUG FACTS

Active Ingredients Purpose

Benzalkonium Chloride 0.15%..........Antimicrobial

Purpose

Antimicrobial

Uses

cleans area around wound, kills bacteria that cause infection and speeds healing

Warnings

For external use on dogs only.

Do not use

- On dogs less than 12 weeks old
- In eyes, over large areas of the body, in cases of deep or punctured wounds, on animal bites, or on serious burns
- If redness, irritation, or swelling persists or increases stop use and consult a veterinarian
- For over one week unless directed by a veterinarian. If condition persists or gets worse, consult a veterinarian

Keep this and all pet products out of reach of children.

Directions

thoroughly cleanse affected area to remove dirt and debris. Rinse well to eliminate any soap residue. Apply lotion twice daily or as needed. Do not wash off. Continue usage until area is completely healed. Wash hands after application.

Other information

avoid temperatures above 86 F

Drug Facts (contiuned)

Inactive ingredients Carbomer, Cetyl Alcohol, Dimethicone, Ethylhexyl Glycerin, Glycerin USP, Glyceryl Acrylate/Acrylic Acid Copolymer, Glyceryl Stearate, Glyceryl Stearate SE, Mineral Oil, PEG-100 Stearate, Perflurodecalin (Rejuvenox), Phenoxyethanol, Propylene Glycol, Stearic Acid, Triethanolamine, Water.

DESCRIPTION

Rejuvenox oxygenates the skin layers which promotes healing.

Rejuvenox is a registered trademark of Melan-Inc.

DOGSWELL.COM

Facebook.com/Dogswell 888-559-8833

Distrubuted by Whitebridge Pet Brands,

St. Louis, MO 63141

2020 Whitebridge. All Rights Reserved.

NDC# 86131-201-04

PACKAGE LABEL

[Image jpeg] REMEDY RECOVERY

DOGSWELL

WOUND & INFECTION MEDICATION

for DOGS

TREATS INFECTIONS

KILLS BACTERIA

PROMOTES HEALING

For Minor Wounds

or Broken Skin

Net Contents: 118ml. (4 fl. oz.)